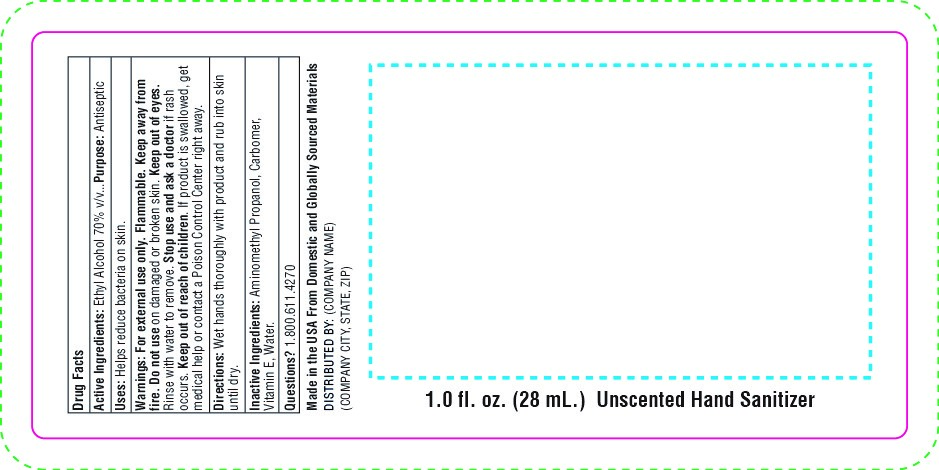 DRUG LABEL: SnugZ Beaded Hand Sanitizer Gel
NDC: 76309-351 | Form: GEL
Manufacturer: SnugZ/USA, LLC
Category: otc | Type: HUMAN OTC DRUG LABEL
Date: 20251229

ACTIVE INGREDIENTS: ALCOHOL 70 mL/100 mL
INACTIVE INGREDIENTS: AMINOMETHYL PROPANEDIOL; ETHYLHEXYL PALMITATE; WATER; CARBOMER 940

ZSB- Beaded Hand Sanitizer Gel

DOSAGE AND ADMINISTRATION

Wet hands thoroughly with product and rub into skin until dry.

WARNINGS

Warnings: For external use only. Flammable, keep away from fire. Do not use on damaged or broken skin. Keep out of eyes. Rinse with water to remove. Stop use and ask a doctor if rash occurs. Keep out of reach of children. If product is swallowed, get medical help or contact a Poison Control Center right away.

Inactive Ingredients: Aminomethyl Propanol, Carbomer, Vitamin E, Water

Active Ingredient: Ethyl Alcohol 70% v/v

Purpose: Antiseptic

Keep out of reach of children.

Indications: Helps reduce bacteria on skin.